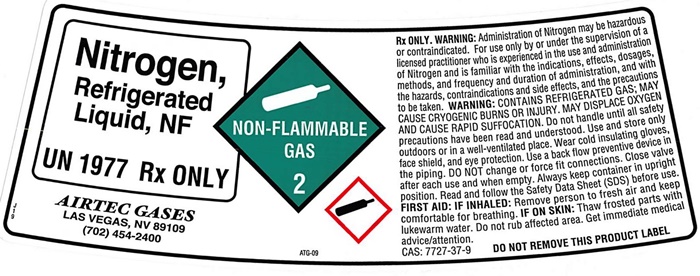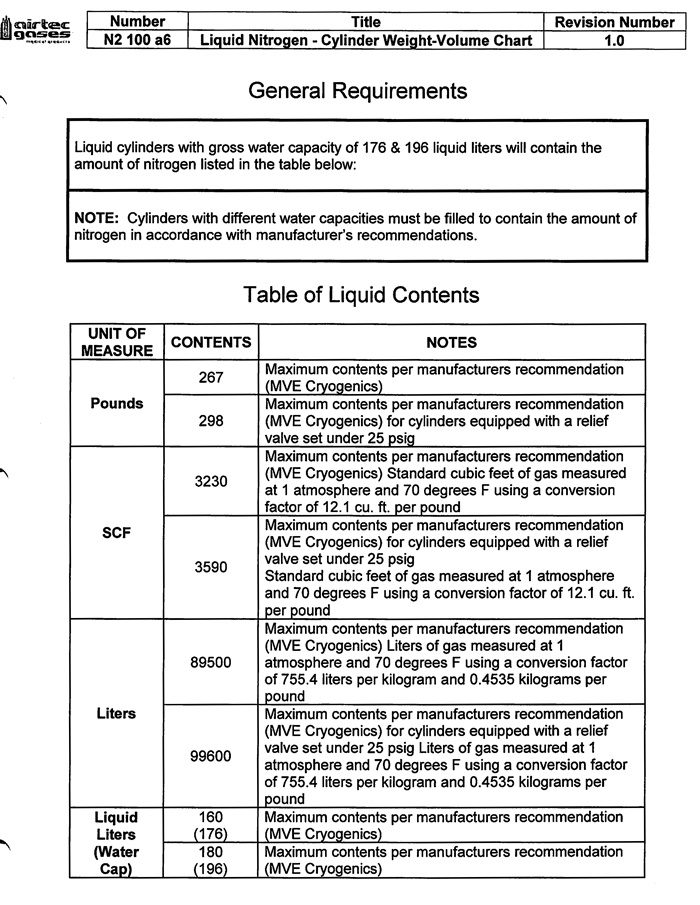 DRUG LABEL: NITROGEN
NDC: 24312-002 | Form: GAS
Manufacturer: Airtec Gases, LLC
Category: prescription | Type: HUMAN PRESCRIPTION DRUG LABEL
Date: 20251013

ACTIVE INGREDIENTS: NITROGEN 99 L/100 L

Nitrogen

NITROGEN REFRIGERATED LIQUID, NF Label

Nitrogen, Refrigerated Liquid, NF

UN1977 Rx ONLY

NON-FLAMMABLE GAS 2 ATG-08

AIRTEC GASES

LAS VEGAS, NV 89109

(702) 454-2400

Rx ONLY. WARNING: Administration of Nitrogen may be hazardous or contraindicated. For use only by or under the supervision of a licensed practitioner who is experienced in the use and administration of Nitrogen and is familiar with the indications, effects, dosages, methods, and frequency and duration of administration, and with the hazards, contraindications, and side effects, and the precautions to be taken.

WARNING: CONTAINS REFRIGERATED GAS; MAY CAUSE CRYOGENIC BURNS OR INUURY. MAY DISPLACE OXYGEN AND CAUSE RAPID SUFFOCATION. Do not handle until all safety precautions have been read and understood. Use and store only outdoors or in a well-ventilated place. Wear cold insulating gloves, face shield, and eye protection. Use a back flow preventive device in the piping. DO NOT change or force fit connections. Close valve after each use and when empty. Always keep container in upright position. Read and follow the Safety Data Sheet (SDS) before use.

FIRST AID: IF INHALED: Remove person to fresh air and keep comfortable for breathing. IF ON SKIN: Thaw frosted parts with lukewarm water. Do not rub affected area. Get immediate medical advice/attention.

CAS: 7727-37-9 DO NOT REMOVE THIS PRODUCT LABEL.

Nitrogen Contents

 | Number | Title | Revision Number
 | N2 100 a6 | Liquid Nitrogen - Cylinder Weight-Volume Chart | 1.0

General Requirements

Liquid cylinders with gross water capacity of 176 & 196 liquid liters will contain the amount of nitrogen listed in the table below:

NOTE: Cylinders with different water capacities must be filled to contain the amount of nitrogen in accordance with manufacturer’s recommendations.

Table of Liquid Contents

UNIT OF MEASURE | CONTENTS | NOTES
Pounds | 267 | Maximum contents per manufacturers recommendation (MVE Cryogenics)
Pounds | 298 | Maximum contents per manufacturers recommendation (MVE Cryogenics) for cylinders equipped with a relief valve set under 25 psig
SCF | 3230 | Maximum contents per manufacturers recommendation (MVE Cryogenics) Standard cubic feet of gas measured at 1 atmosphere and 70 degrees F using a conversion factor of 12.1 cu. ft. per pound
SCF | 3590 | Maximum contents per manufacturers recommendation (MVE Cryogenics) for cylinders equipped with a relief valve set under 25 psig; Standard cubic feet of gas measured at 1 atmosphere and 70 degrees F using a conversion factor of 12.1 cu. ft. per pound
Liters | 89500 | Maximum contents per manufacturers recommendation (MVE Cryogenics) Liters of gas measured at 1 atmosphere and 70 degrees F using a conversion factor of 755.4 liters per kilogram and 0.4535 kilograms per pound
Liters | 99600 | Maximum contents per manufacturers recommendation (MVE Cryogenics) for cylinders equipped with a relief valve set under 25 psig Liters of gas measured at 1 atmosphere and 70 degrees F using a conversion factor of 755.4 liters per kilogram and 0.4535 kilograms per pound
Liquid Liters; (Water Cap) | 160; (176) | Maximum contents per manufacturers recommendation (MVE Cryogenics)
Liquid Liters; (Water Cap) | 180; (196) | Maximum contents per manufacturers recommendation (MVE Cryogenics)